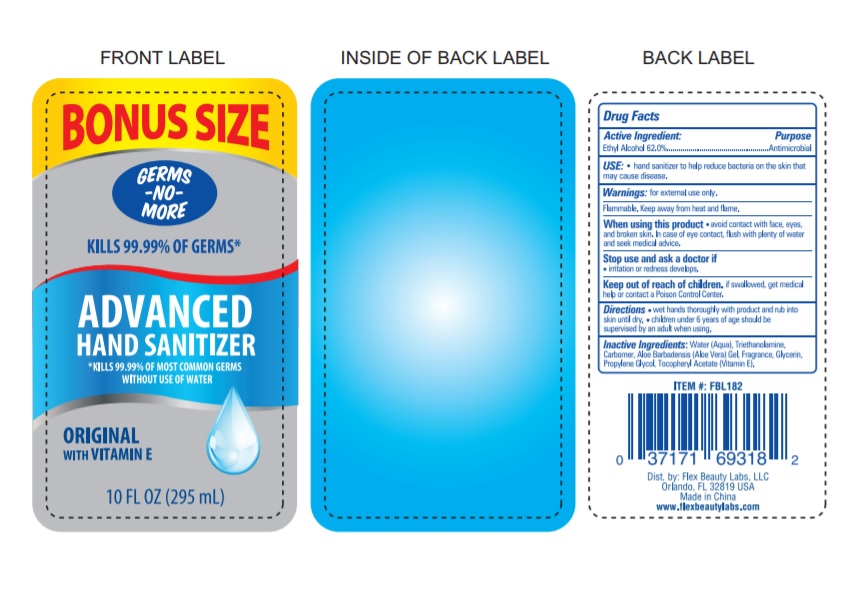 DRUG LABEL: Advanced Hand Sanitizer
NDC: 72308-001 | Form: LIQUID
Manufacturer: Flex Beauty Labs, LLC
Category: otc | Type: HUMAN OTC DRUG LABEL
Date: 20180507

ACTIVE INGREDIENTS: ALCOHOL 62 mL/1 mL
INACTIVE INGREDIENTS: ALOE VERA LEAF; CARBOXYPOLYMETHYLENE; GLYCERIN; PROPYLENE GLYCOL; .ALPHA.-TOCOPHEROL ACETATE; TROLAMINE; WATER

Drug Facts Active Ingredient

Ethyl Alcohol 62.0%

Purpose

Antimicrobial

Uses

Hand Santizer to help reduce bacteria on skin that may cause disease.

Warnings

Flammable. Keep away from heat or flame.

For external use only.

When using this product,

do not use in or near the eyes. In case of contact, rinse eyes thoroughtly with water. Stop use and ask doctor if irritation or rash appears and lasts. Keep out of reach for children.

If swallowed, get medical help or contact a Posion Control Center right away.

Directions:

. Place enough Product in your palm to thoroughtly spread on both hands and rub into the skin until dry.

. Children under 6 years of age should be supervised when using this product.

Other Information:

. Store below 106℉. (41℃)

Inactive Ingredients:

Water (Aqua), Aloe Vera Leaf , Carbomer, Fragrance, Glycerin, Propylene Glycol, Tocopheryl Acetate (Vitamin E), Triethanolamine,